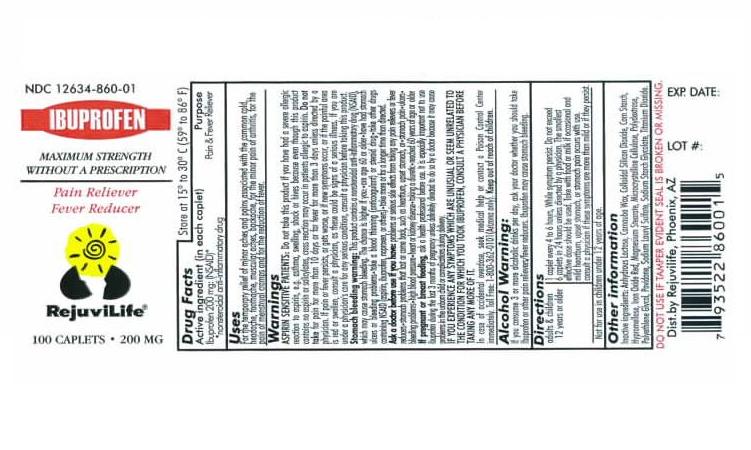 DRUG LABEL: IBUPROFEN
NDC: 12634-860 | Form: TABLET
Manufacturer: Apotheca Inc.
Category: otc | Type: HUMAN OTC DRUG LABEL
Date: 20100219

ACTIVE INGREDIENTS: IBUPROFEN 200 mg/1 1
INACTIVE INGREDIENTS: ANHYDROUS LACTOSE; CARNAUBA WAX; SILICON DIOXIDE; HYPROMELLOSE; MAGNESIUM STEARATE; CELLULOSE, MICROCRYSTALLINE; POVIDONE; SODIUM LAURYL SULFATE; STARCH, CORN; TITANIUM DIOXIDE

Ibuprofen Tablets, USP (NSAID)Pain Reliever/ Fever Reducer DRUG FACTS

ACTIVE INGREDIENT

(in each Tablet)

Ibuprofen 200 mg (NSAID)**

**nonsteroidal anti-inflammatory drug

PURPOSE

Pain reliever/fever reducer

USES

- temporarily relieves minor aches and pains due to:
- headache
- muscular aches
- minor pain or arthritis
- toothache
- backache
- the common cold
- menstrual cramps
- temporarily reduces fever

WARNINGS

Allergy alert:

Ibuprofen may cause a severe allergic reaction, especially in people allergic to aspirin. Symptoms may include:

- hives
- facial swelling
- asthma (wheezing)
- shock
- skin reddening
- rash
- blisters

If an allergic reaction occurs, stop use and seek medical help right away.

Alcohol Warning: If you consume 3 or more alcohol drinks per day, ask your Doctor whether you should take Ibuprofen or other pain relievers/fever reducers.

Stomach bleeding warning: This product contains a nonsteroidal anti-inflammatory drug (NSAID), which may cause stomach bleeding. The chance is higher if you:

- are age 60 or older
- have had stomach ulcers or bleeding problems
- take a blood thinning (anticoagulant) or steroid drug
- take other drugs containing NSAID (aspirin, ibuprofen, naproxen, or others)
- have 3 or more alcoholic drinks every day while using this product
- take more or for a longer time than directed

DO NOT USE

- if you have ever had an allergic reaction to any other pain reliever/fever reducer
- right before or after heart surgery

ASK DOCTOR

Ask a doctor before use if you have

- problems or serious side effects from taking pain relievers or fever reducers
- stomach problems that last or come back, such as heartburn, upset stomach, or stomach pain
- ulcers
- bleeding problems
- high blood pressure
- heart or kidney disease
- taken a diuretic
- reached age 60 or older

Ask a doctor before use if you are

- taking aspirin for heart attack or stroke because ibuprofen may decrease this benefit of aspirin
- taking any other drug containing an NSAID (prescription or nonprescription)
- taking a blood thinning (anticoagulant) or steroid drug
- under a doctor's care for any serious condition
- taking any other drug
- consuming 3 or more alcohol drinks per day

WHEN USING THIS PRODUCT

- take with food or milk if stomach upset occurs
- long term continuous use ay increase the risk of heart attack or stroke

STOP USE AND ASK A DOCTOR IF

- you feel faint, vomit blood, or have bloody or black stools. These are signs of stomach bleeding.
- pain gets worse or lasts more than 10 days
- fever gets worse or lasts more than 3 days
- stomach pain or upset gets worse or lasts
- redness or swelling is present in the painful area
- any new symptoms appear

IF PREGNANT OR BREAST-FEEDING

- ask a health professional before use. It is especially important not to use ibuprofen during the last 3 months of pregnancy unless definitely directed to do so by a doctor because it may cause problems in the unborn child or complications during delivery.

KEEP OUT OF REACH OF CHILDREN

In case of overdose, get medical help or contact a Poison Control Center 1-800-362-0101 (Arizona only) immediately.

DIRECTIONS

- do not take longer than 10 days, unless directed by a doctor (see Warnings)

Adults and children 12 years and older | - take 1 caplet every 4 to 6 hours while symptoms persist - if pain or fever does not respond to 1 caplet, 2 caplets may be used - do not exceed 6 caplets in a 24-hour period, unless directed by a physician - take with food or milk, if occasional and mild heartburn, upset stomach, or stomach pain occurs with use - consult a physician if these symptoms are more thsn mild or if they persist
Children under 12 years | - not for use

OTHER INFORMATION

- store at 15 – 30°C (59-86°F).

Inactive ingredients

Anhydrous Lactose, Carnauba Wax, Colloidal Silicon Dioxide, Hypromellose, Iron Oxide Red, Magnesium Stearate, Microcrystalline Cellulose, Polydextrose, Polyethylene Glycol, Povidone, Sodium Lauryl Sulfate, Sodium Starch Glycolate, Corn Starch, Titanium Dioxide.

QUESTIONS OR COMMENTS

Call 1-800-262-5244

Monday though Friday 9AM – 2PM MST

Distributed by:

RejuviLife, Phoenix, AZ

RejuviLife is a trademark of Apotheca Inc.

PACKAGE LABEL,PRINCIPAL DISPLAY PANEL,ADDITIONAL LABELS UPON REQUEST

NDC 12634-860-01

IBUPROFEN

MAXIMUM STRENGTH
WITHOUT A PRESCRIPTION

Pain Reliever
Fever Reducer

RejuviLife®

100 CAPLETS

200 MG